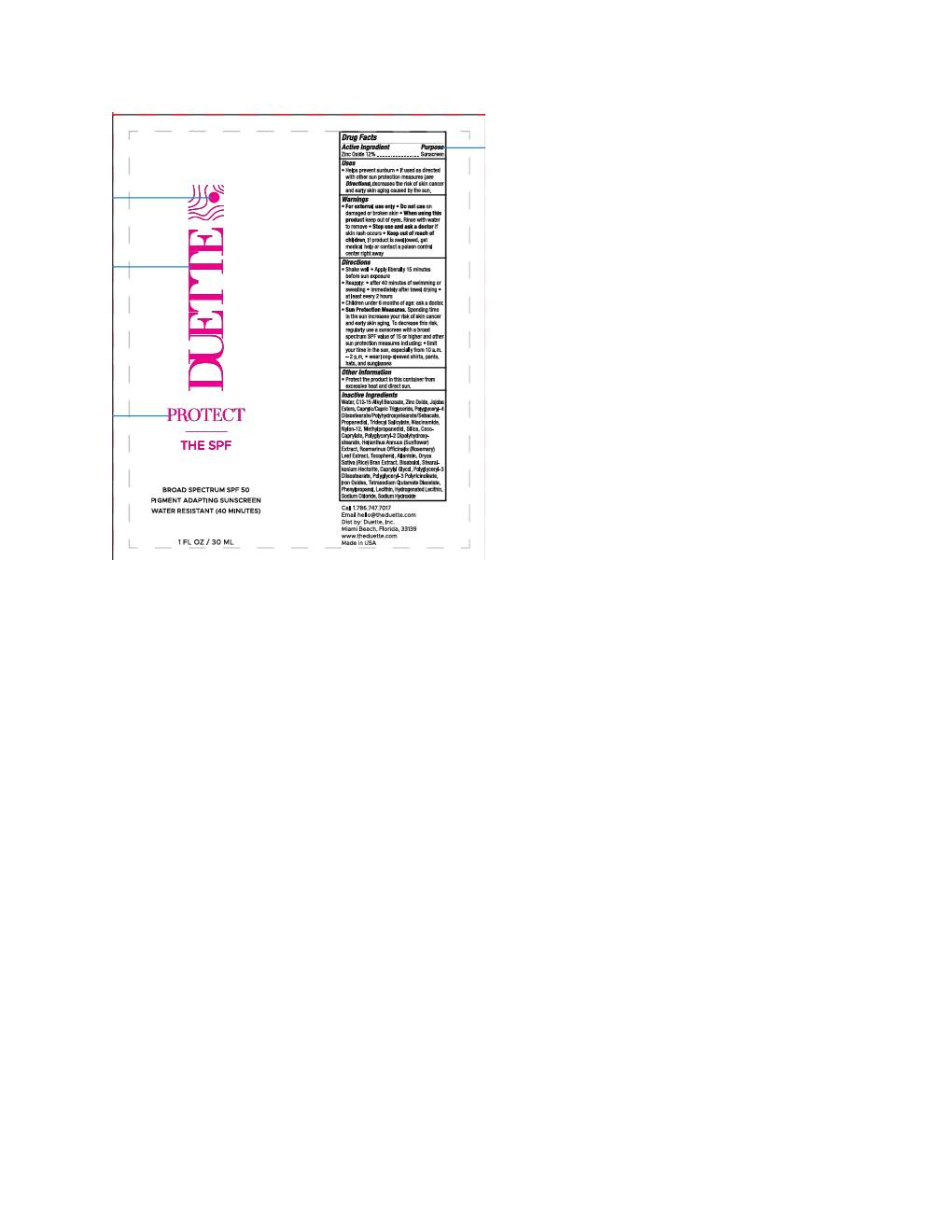 DRUG LABEL: Duette Tinted
NDC: 84123-2034 | Form: LOTION
Manufacturer: Skin Theory Studios
Category: otc | Type: HUMAN OTC DRUG LABEL
Date: 20251106

ACTIVE INGREDIENTS: ZINC OXIDE 132 mg/1 mL
INACTIVE INGREDIENTS: STEARALKONIUM HECTORITE; JOJOBA OIL; ORYZA SATIVA WHOLE; TRIDECYL SALICYLATE; SILICON DIOXIDE; TOCOPHEROL; POLYGLYCERYL-3 DIISOSTEARATE; CAPRYLYL GLYCOL; COCO-CAPRYLATE; NYLON-12; PHENYLPROPANOL; FERRIC OXIDE RED; FERRIC OXIDE YELLOW; FERROSOFERRIC OXIDE; HELIANTHUS ANNUUS FLOWERING TOP; LECITHIN, SOYBEAN; METHYLPROPANEDIOL; POLYGLYCERYL-2 DIPOLYHYDROXYSTEARATE; ALLANTOIN; ALKYL (C12-15) BENZOATE; ROSMARINUS OFFICINALIS FLOWER; .ALPHA.-BISABOLOL, (+)-; SODIUM HYDROXIDE; WATER; NIACINAMIDE; PROPANEDIOL; TETRASODIUM GLUTAMATE DIACETATE; SODIUM CHLORIDE; POLYGLYCERYL-4 DIISOSTEARATE/POLYHYDROXYSTEARATE/SEBACATE

Duette Tinted